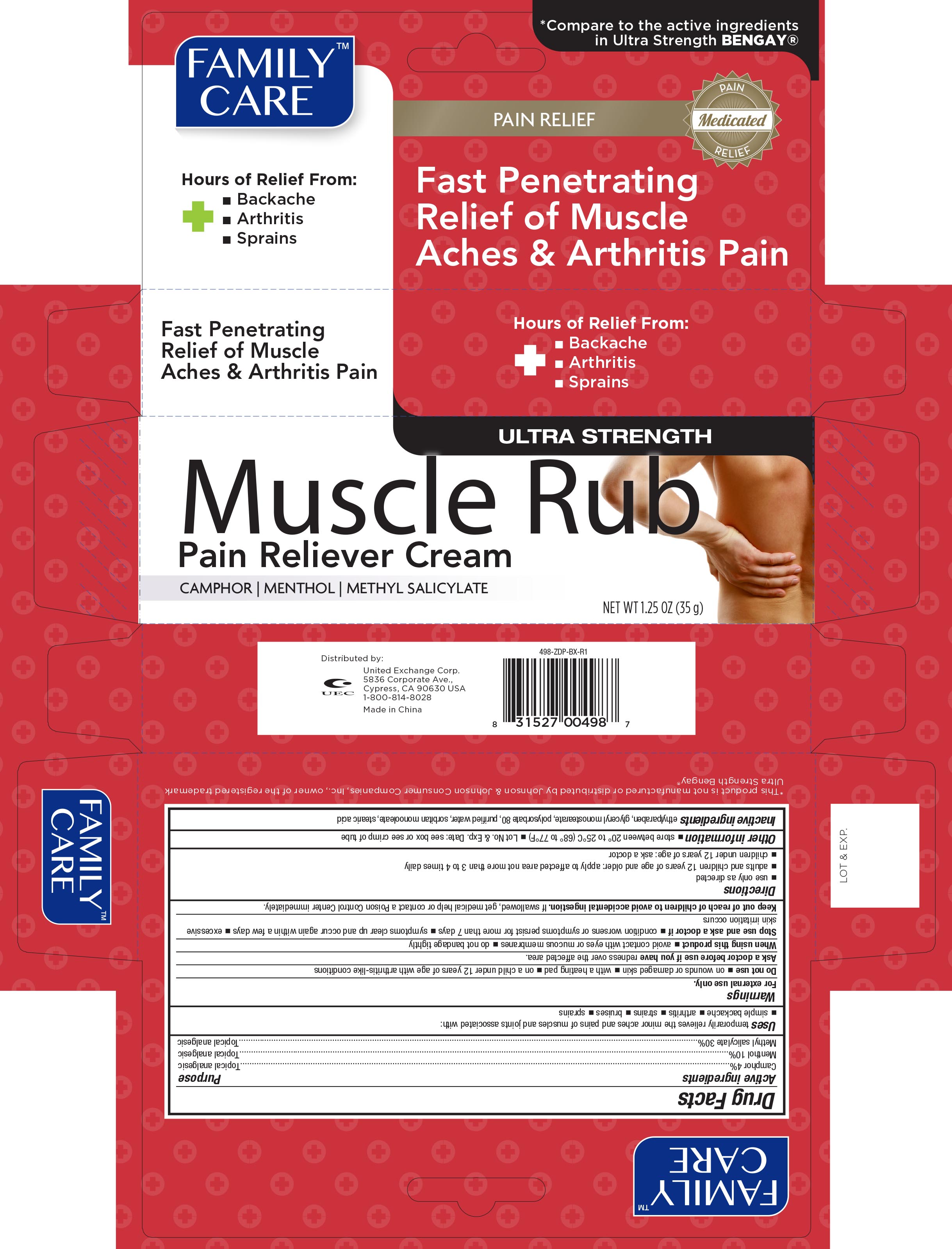 DRUG LABEL: Family Care Muscle Rub
NDC: 65923-987 | Form: CREAM
Manufacturer: United Exchange Corp.
Category: otc | Type: HUMAN OTC DRUG LABEL
Date: 20251022

ACTIVE INGREDIENTS: CAMPHOR (SYNTHETIC) 40 mg/1 g; MENTHOL, UNSPECIFIED FORM 100 mg/1 g; METHYL SALICYLATE 300 mg/1 g
INACTIVE INGREDIENTS: SORBITAN MONOOLEATE; ETHYLPARABEN; GLYCERYL MONOSTEARATE; POLYSORBATE 80; WATER; STEARIC ACID

Family Care Pain Relieving Muscle Rub Cream 1.25 oz 498 Dingtai

Active ingredients Purpose

Camphor 4%......................................................................Topical analgesic

Menthol 10%......................................................................Topical analgesic

Methyl salicylate 30%.........................................................Topical analgesic

Uses

temporarily relieves the minor aches and pains of muscles and joints associated with:

- simple backache
- arthritis
- strains
- bruises
- sprains

Warnings

For external use only.

Do not use

- on wounds or damaged skin
- with a heating pad
- on a child under 12 years of age with arthritis-like conditions

Ask a doctor before use if you have redness over the affected area

When using this product

- avoid contact with eyes or mucous membranes
- do not bandage tightly

Stop use and ask a doctor if

- condition worsens or symptoms persist for more than 7 days
- symptoms clear up and occur again within a few days
- excessive skin irritation occurs

Keep out of reach of children to avoid accidental ingestion. If swallowed, get medical help or contact a Poison Control Center immediately.

Directions

- use only as directed
- adults and children 12 years of age and older: apply to affected area not more than 3 to 4 times daily
- children under 12 years of age: ask a doctor

Other information

- store between 20° to 25°C (68° to 77°F)
- Lot No. & Exp. Date: see box or see crimp of tube

Inactive ingredients

ethylparaben, glyceryl monostearate, polysorbate 80, purified water, sorbitan monooleate, stearic acid

DOSAGE AND ADMINISTRATION

Distributed by:

United Exchange Corp.

5836 Corporate Ave.

Cypress, CA 90630

1-800-814-8028

Made in China